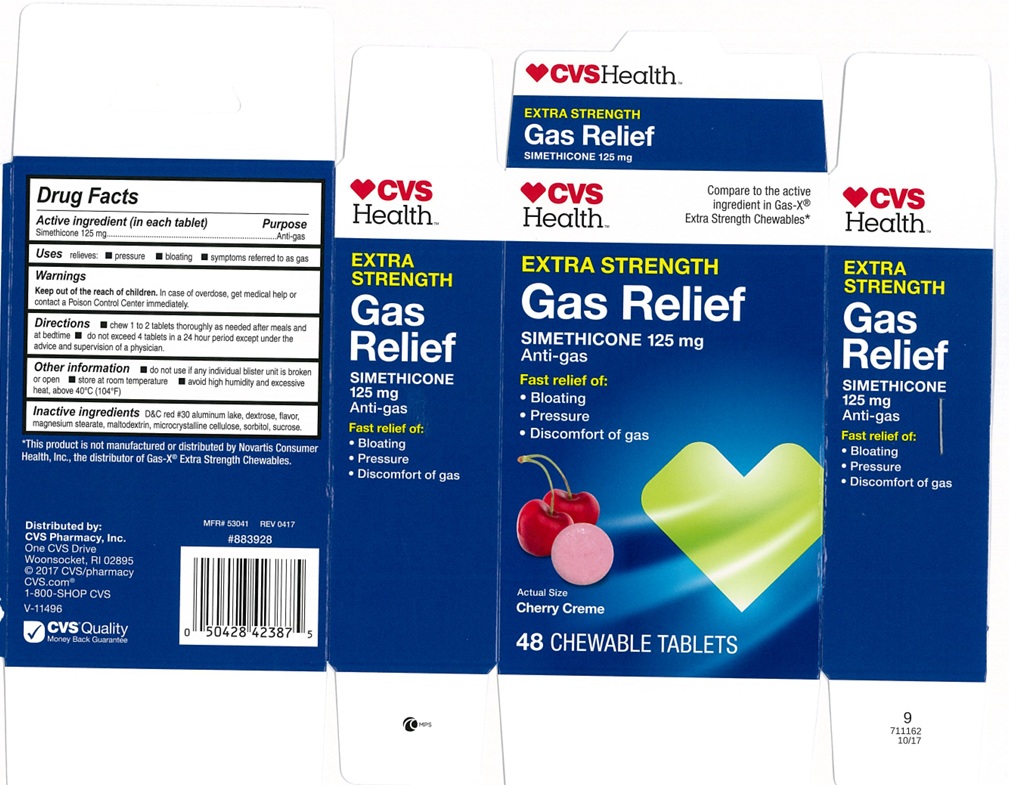 DRUG LABEL: Extra Strength Gas Relief Cherry Creme
NDC: 51316-134 | Form: TABLET, CHEWABLE
Manufacturer: CVS
Category: otc | Type: Human OTC Drug Label
Date: 20250127

ACTIVE INGREDIENTS: DIMETHICONE 125 mg/1 1
INACTIVE INGREDIENTS: D&C RED NO. 30 ALUMINUM LAKE; MAGNESIUM STEARATE; CELLULOSE, MICROCRYSTALLINE; SORBITOL; SUCROSE; MALTODEXTRIN; DEXTROSE, UNSPECIFIED FORM

Extra Strength Gas Relief 134CHR

ACTIVE INGREDIENT(S)

Simethicone 125 mg

PURPOSE

Anti-gas

USE(S)

relieves:

- Pressure
- bloating
- Symptoms referred to as gas

WARNINGS

.

KEEP OUT OF THE REACH OF CHILDREN.

In case of overdose, get medical help or contact a Poison Control Centre immediately.

DIRECTIONS

- chew 1 to 2 tablets thoroughly as needed after meals and at bedtime
- do not exceed 4 tablets in a 24 hour period except under the advice and supervision of a physician.

OTHER INFORMATION

- do not use if any individual blister unit is broken or open
- store at room temperature
- avoid high humidity and excessive heat, above 40ºC (104ºF)

INACTIVE INGREDIENTS

D&C red #30 aluminum lake, dextrose, flavor, magnesium stearate, maltodextrin, microcrystalline cellulose, sorbitol, sucrose.

PRINCIPAL DISPLAY PANEL

CVS Health

NDC 51316-134-13

Compare to the active ingredient in Gas-X® Extra Strength Chewables*

EXTRA STRENGTH

Gas Relief

SIMETHICONE 125 mg

Anti-gas

fast relief of:

- Bloating
- Pressure
- Discomfort of gas

cherry creme

48 chewable tablets